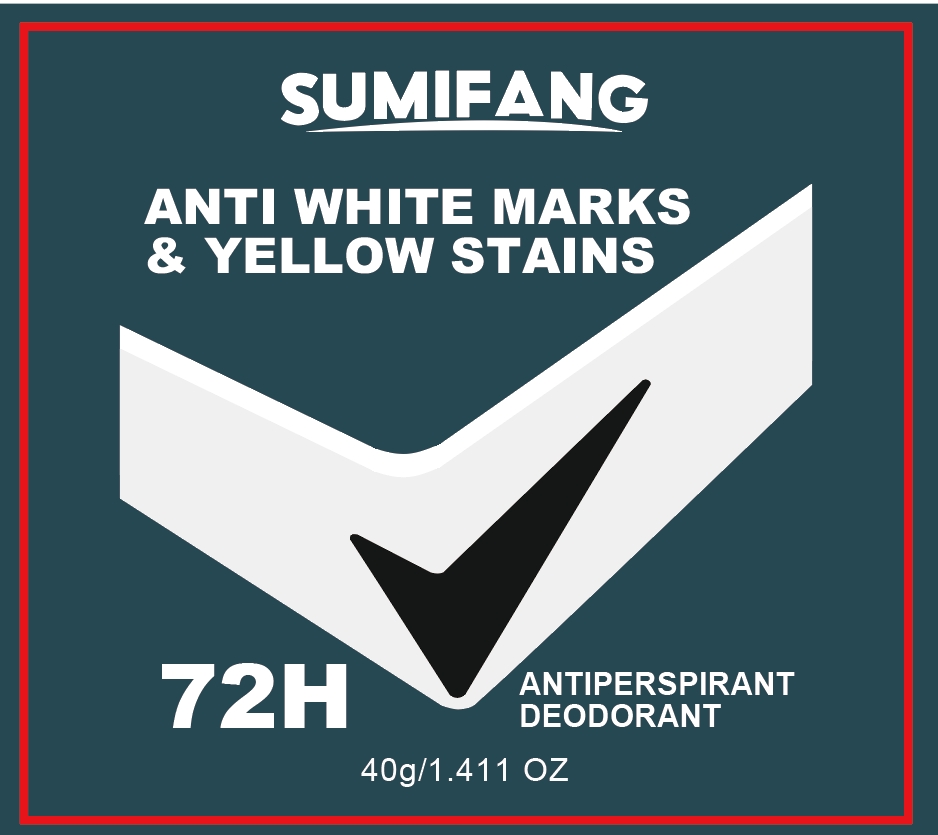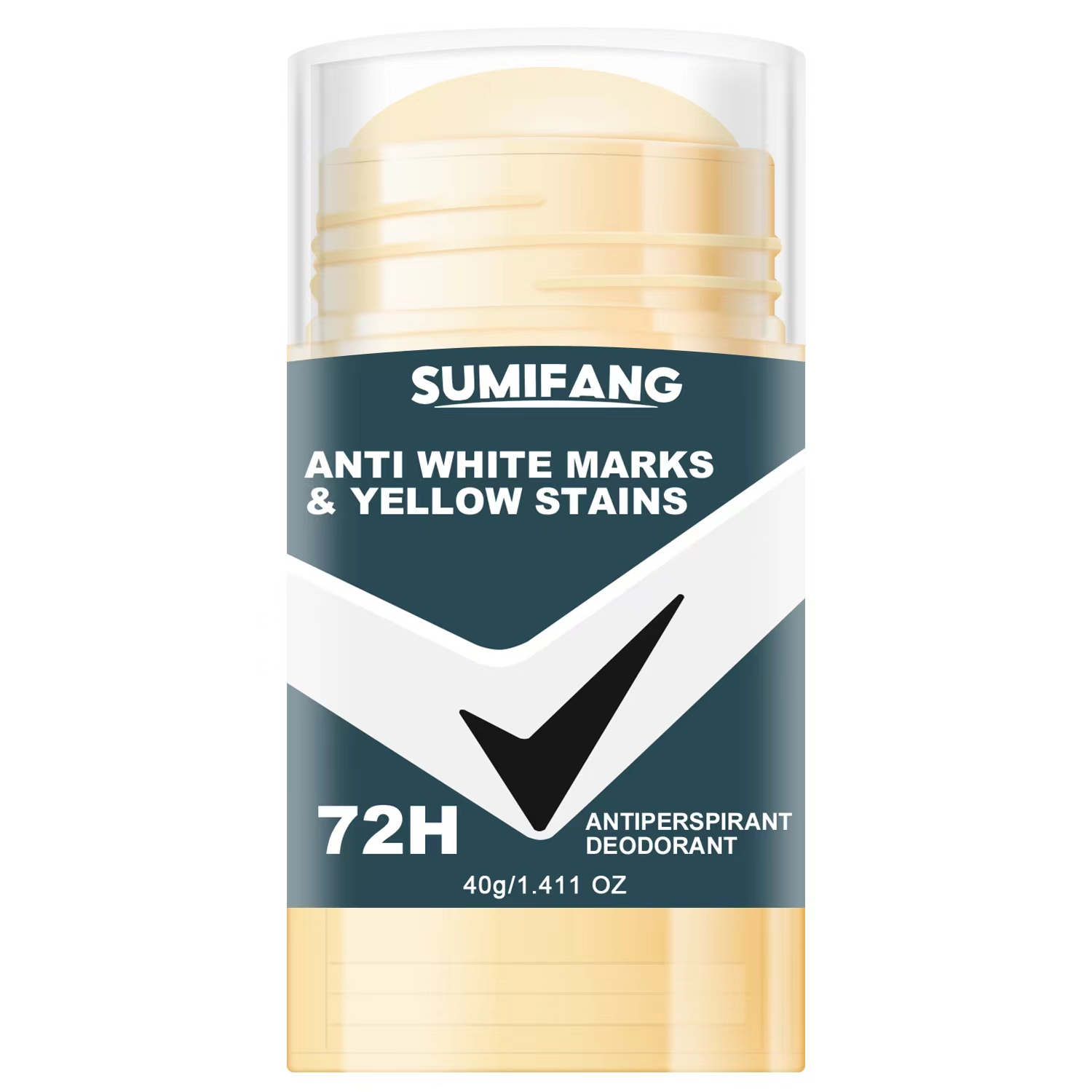 DRUG LABEL: 72H BODY HEAT
NDC: 84025-061 | Form: POULTICE
Manufacturer: Guangzhou Yanxi Biotechnology Co., Ltd
Category: otc | Type: HUMAN OTC DRUG LABEL
Date: 20240710

ACTIVE INGREDIENTS: HYDROGENATED AVOCADO OIL 4 mg/40 g; UREA C-13 2 mg/40 g
INACTIVE INGREDIENTS: WATER

DOSAGE AND ADMINISTRATION

For general body deodorization.

WARNINGS

Keep out of Children

INACTIVE INGREDIENT

Aqua

INDICATIONS AND USAGE

For general body deodorization.

Keep out of Children

PURPOSE

Preventing sweating